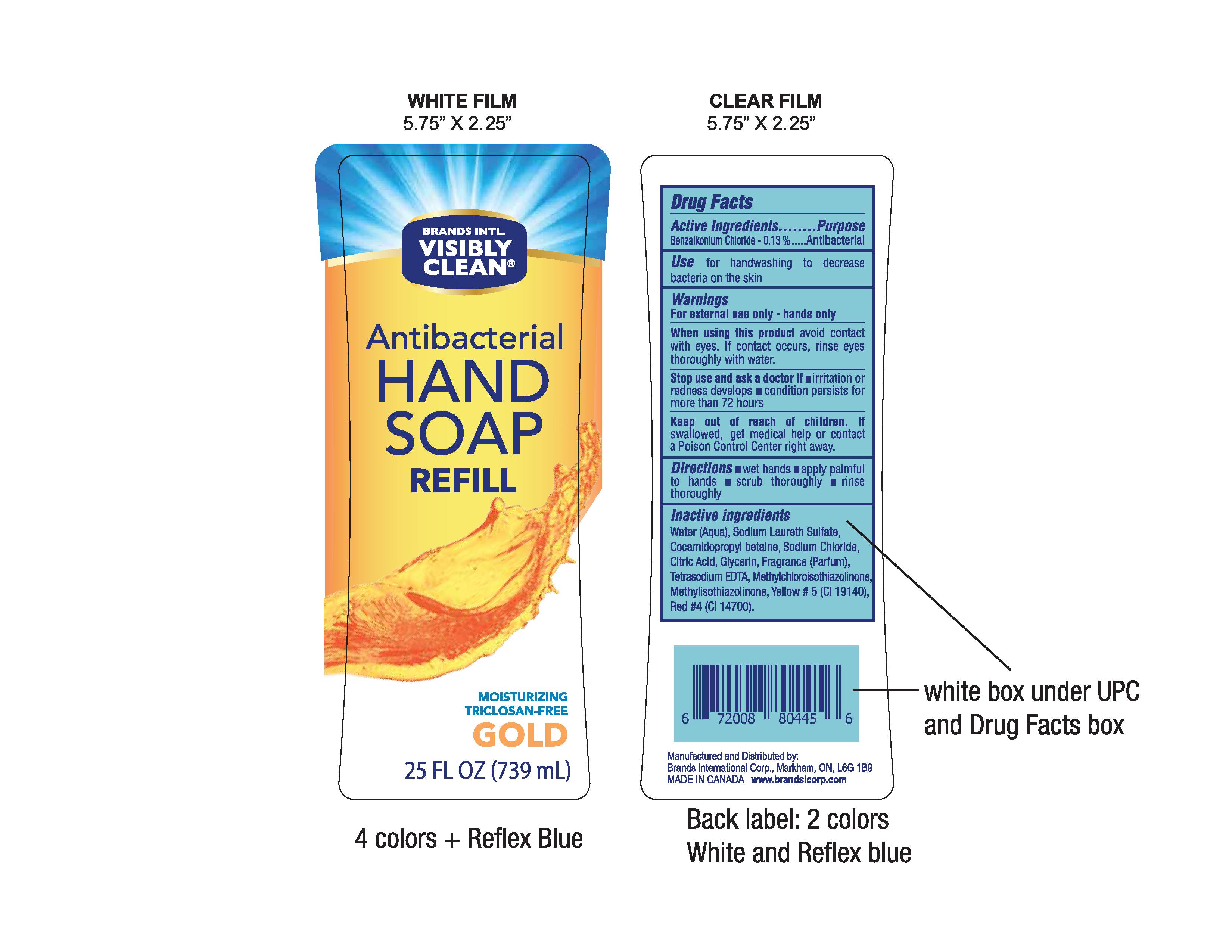 DRUG LABEL: Benzalkonium Chloride
NDC: 50157-206 | Form: LIQUID
Manufacturer: Brands International Corporation
Category: otc | Type: HUMAN OTC DRUG LABEL
Date: 20161003

ACTIVE INGREDIENTS: BENZALKONIUM CHLORIDE 1.3 mg/1 mL
INACTIVE INGREDIENTS: WATER; SODIUM LAURETH SULFATE; SODIUM CHLORIDE; ANHYDROUS CITRIC ACID; GLYCERIN; DITETRACYCLINE TETRASODIUM EDETATE; METHYLCHLOROISOTHIAZOLINONE; METHYLISOTHIAZOLINONE; FD&C YELLOW NO. 5; FD&C RED NO. 4; COCAMIDOPROPYL BETAINE

Antibacterial Hand Soap Refill

ACTIVE INGREDIENT

Benzalkonium Chloride - 0.13%

Purpose - Antibacterial

INDICATIONS AND USAGE

Use for handwashing to decrease bacteria on the skin

WARNINGS

Warning - For external use only - hands only

When using this product avoid contact with eyes. If contact occurs, rinse eyes thoroughly with water

Stop use and ask a doctor if

- irritaion or redness develops
- condition persists for more than 72 hours

Keep out of reach of children. If swallowed, get medical help or contact a Poison Control Center right away

Directions

- Wet Hands
- Apply palmful to hands
- scrub thoroughly
- rinse thoroughly

INACTIVE INGREDIENT

Inactive Ingredients: Water (Aqua), Sodium Laureth Sulfate, Cocamidopropyl Betaine, Sodium Chloride, Citrtic Acid, Glycerin, Fragrance (Parfum), Tetrasodium EDTA, Methylchloroisothiazolinone, Methylisothiazolinone, Yellow# 5 (Cl 19140), Red# 4 (Cl 14700)